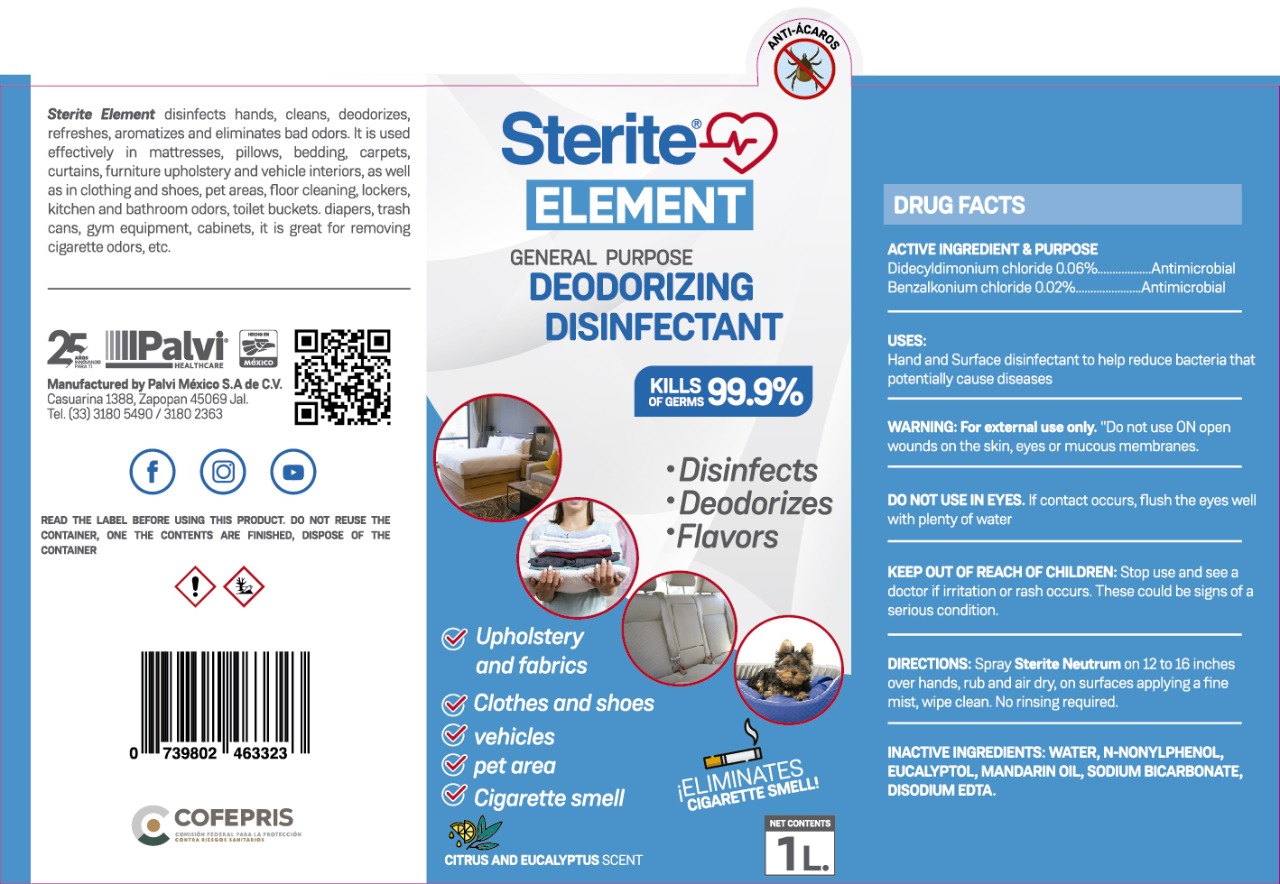 DRUG LABEL: STERITE ELEMENT
NDC: 81576-2000 | Form: LIQUID
Manufacturer: PALVI MEXICO, S.A. DE C.V.
Category: otc | Type: HUMAN OTC DRUG LABEL
Date: 20210216

ACTIVE INGREDIENTS: BENZALKONIUM CHLORIDE 0.002 mg/1 mL; DIDECYLDIMONIUM CHLORIDE 0.006 mg/1 mL
INACTIVE INGREDIENTS: ACID GREEN 50 0.0105 mL/1 mL; EDETATE DISODIUM 0.0003 mL/1 mL; LEMON OIL 0.003 mL/1 mL; SODIUM BICARBONATE 0.005 mL/1 mL; WATER 0.9482 mL/1 mL; N-NONYLPHENOL (MIXED ISOMERS) 0.025 mL/1 mL

STERITE ELEMENT SANITIZER

ACTIVE INGREDIENT SECTION

DIDECYLDIMONIUM CHLORIDE

BENZALKONIUM CHLORIDE

PURPOSE SECTION

PURPOSE

ANTIMICROBIAL

INDICATIONS AND USAGE SECTION

USES

HAND AND SURGACE DISINFECTANT TO HELP REDUCE BACTERIA THAT POTENTIALLY CAUSE DISEASES

DOSAGE AND ADMINISTRATION SECTION

DIRECTIONS SPRAY STERITE NEUTRUM ON 12 TO 16 INCHES OVER HANDS, RUB AND AIR DRY, ON SURFACES APPLYING A FINE MIST, WIPE CLEAN. NO RINSING REQUIRED.

KEEP OUT OF REACH OF CHILDREN SECTION

KEEP OUT OF REACH OF CHILDREN

WARNINGS AND PRECAUTIONS SECTION

DO NOT USE ON OPEN WOUNDS ON THE SKIN, EYES OR MUCOUS MEMBRANES

WARNINGS SECTION

DO NOT USE IN EYES. IF CONTACT OCCURS, FLUSH THE EYES WELL WITH PLENTY OF WATER.

STOP USE SECTION

STOP USE AND SEE A DOCTOR IF IRRITATION OR RASH OCCURS

INACTIVE INGREDIENTS

INACTIVE INGREDIENTS: WATER N-NONYLPHENOL, EUCALYPTOL, MANDARIN OIL, SODIUM BICARBONATE, DISODIUM EDTA.